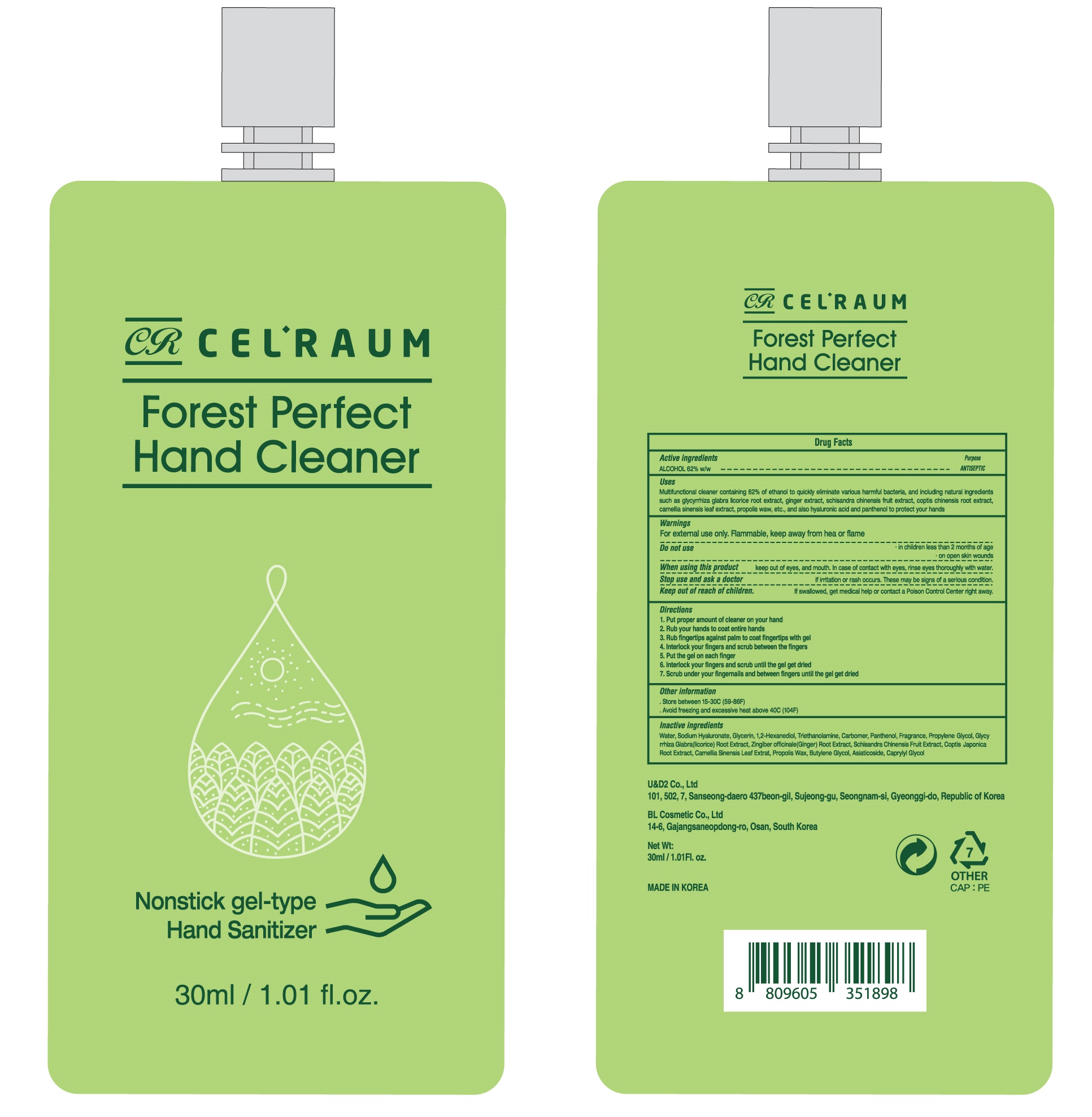 DRUG LABEL: Celraum Forest Perfect Hand Cleaner
NDC: 75368-030 | Form: GEL
Manufacturer: U&D2 Co.,Ltd.
Category: otc | Type: HUMAN OTC DRUG LABEL
Date: 20200608

ACTIVE INGREDIENTS: ALCOHOL 62 mL/100 mL
INACTIVE INGREDIENTS: WATER; HYALURONATE SODIUM; Glycerin; 1,2-Hexanediol; TROLAMINE; CARBOMER HOMOPOLYMER, UNSPECIFIED TYPE; Panthenol; PROPYLENE GLYCOL; GLYCYRRHIZA GLABRA; GINGER; SCHISANDRA CHINENSIS FRUIT; COPTIS JAPONICA ROOT; GREEN TEA LEAF; Propolis Wax; BUTYLENE GLYCOL; Asiaticoside; Caprylyl Glycol

ACTIVE INGREDIENT

ALCOHOL 62% w/w

INACTIVE INGREDIENT

Water, Sodium Hyaluronate, Glycerin, 1,2-Hexanediol, Triethanolamine, Carbomer, Panthenol, Fragrance, Propylene Glycol, Glycyrrhiza Glabra (licorice) Root Extract, Zingiber Officinale (Ginger) Root Extract, Schisandra Chinensis Fruit Extract, Coptis Japonica Root Extract, Camellia Sinensis Leaf Extract, Propolis Wax, Butylene Glycol, Asiaticoside, Caprylyl Glycol

PURPOSE

ANTISEPTIC

WARNINGS

For external use only. Flammable. Keep away from heat or flame
--------------------------------------------------------------------------------------------------------
Do not use
• in children less than 2 months of age
• on open skin wounds
--------------------------------------------------------------------------------------------------------
When using this product keep out of eyes, ears, and mouth. In case of contact with eyes, rinse eyes thoroughly with water.
--------------------------------------------------------------------------------------------------------
Stop use and ask a doctor if irritation or rash occurs. These may be signs of a serious condition.

KEEP OUT OF REACH OF CHILDREN

If swallowed, get medical help or contact a Poison Control Center right away.

Uses

Multifunctional cleaner containing 62% of ethanol to quickly eliminate various harmful bacteria, and including natural ingredients such as glycyrrhiza glabra licorice root extract, ginger extract, schisandra chinensis fruit extract, coptis chinensis root extract, camellia sinensis leaf extract, propolis wax, etc., and also hyaluronic acid and panthenol to protect your hands.

Directions

1. Put proper amount of cleaner on your hand

2. Rub your hands to coat entire hands
3. .Rub fingertips against palm to coat fingertips with gel
4. Interlock your fingers and scrub between the fingers
5. Put the gel on each finger
6. Interlock your fingers and scrub until the gel get dried
7. Scrub under your fingernails and between fingers until the gel get dried

Other information

• Store between 15-30C (59-86F)

• Avoid freezing and excessive heat above 40C (104F)